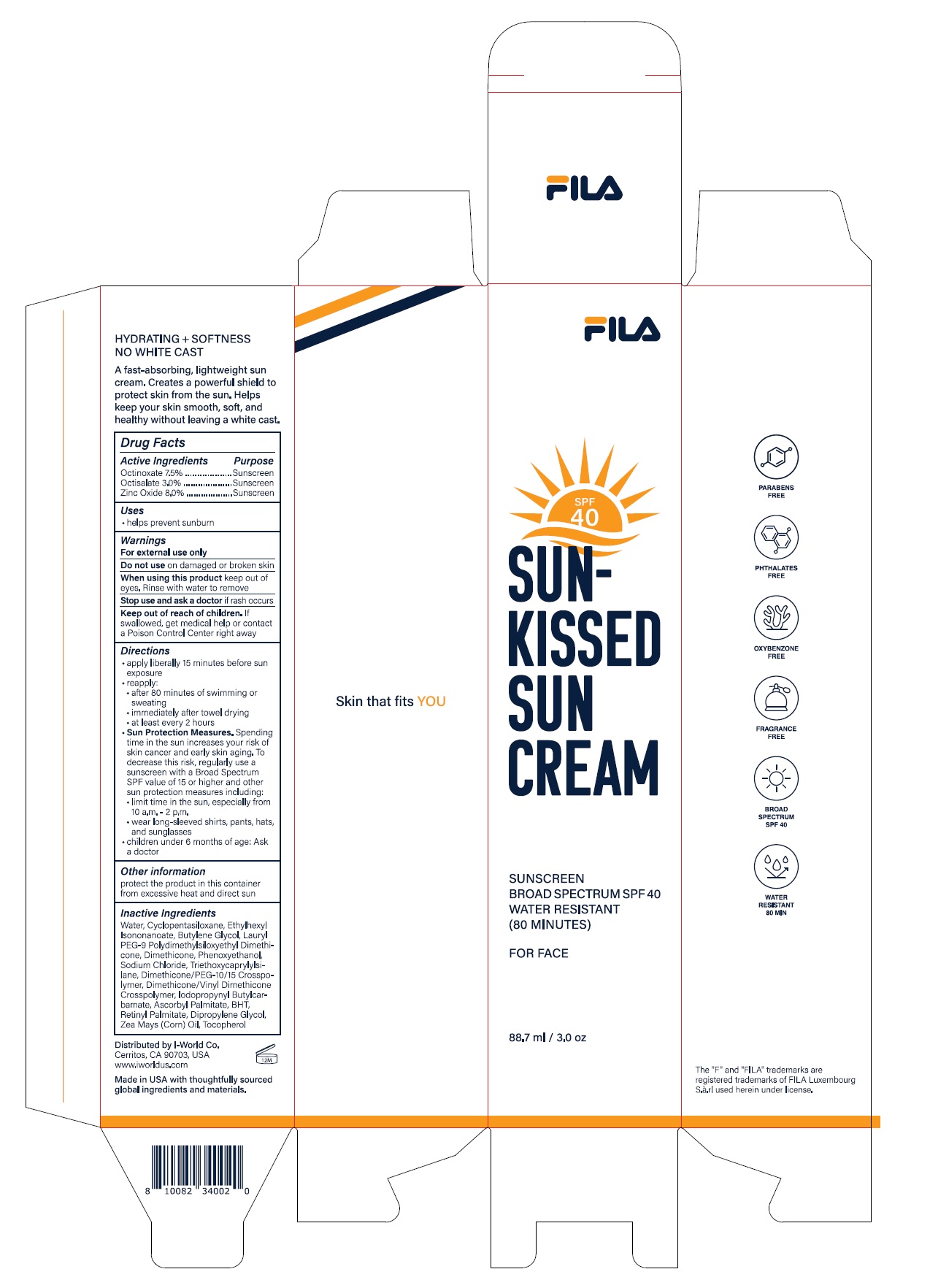 DRUG LABEL: Sun-Kissed Suncream
NDC: 78493-001 | Form: CREAM
Manufacturer: LEE & GEN GLOBAL CORPORATION
Category: otc | Type: HUMAN OTC DRUG LABEL
Date: 20220505

ACTIVE INGREDIENTS: ZINC OXIDE 8 g/100 mL; OCTINOXATE 7.5 g/100 mL; OCTISALATE 3 g/100 mL
INACTIVE INGREDIENTS: WATER; CYCLOMETHICONE 5; ETHYLHEXYL ISONONANOATE; BUTYLENE GLYCOL; LAURYL PEG-9 POLYDIMETHYLSILOXYETHYL DIMETHICONE; DIMETHICONE; PHENOXYETHANOL; SODIUM CHLORIDE; TRIETHOXYCAPRYLYLSILANE; DIMETHICONE/PEG-10/15 CROSSPOLYMER; DIMETHICONE/VINYL DIMETHICONE CROSSPOLYMER (HARD PARTICLE); IODOPROPYNYL BUTYLCARBAMATE; ASCORBYL PALMITATE; BUTYLATED HYDROXYTOLUENE; VITAMIN A PALMITATE; DIPROPYLENE GLYCOL; CORN OIL; TOCOPHEROL

78493-001 Sun-Kissed Suncream

ACTIVE INGREDIENT

OCTINOXATE 7.5%
OCTISALATE 3.0%
ZINC OXIDE 8.0%

PURPOSE

Sunscreen

INDICATIONS AND USAGE

Helps prevent sunburn

DOSAGE AND ADMINISTRATION

For sunscreen use:
■ apply liberally 15 minutes before sun exposure
■ reapply: after 80 minutes of swimming or sweating, immediately after towel drying, at least every 2 hours.
■ Sun Protection Measures.Spending time in the sun increases your risk of skin cancer and early skin aging. To decrease this risk, regularly use a sunscreen with a Broad Spectrum SPF value of 15 or higher and other sun protection measures including:
– limit time in the sun, especially from 10 a.m. – 2 p.m.
– wear long-sleeved shirts, pants, hats and sunglasses
■ children under 6 months of age: ask a doctor

WARNINGS

For external use only.
Do not use on damaged or broken skin.
When using this product, keep out of eyes. Rinse with water to remove.
Stop using and ask a doctor if rash occurs.

KEEP OUT OF REACH OF CHILDREN

Keep out of reach of the children. If product is swallowed, get medical help or contact a poison control center right away.

INACTIVE INGREDIENT

Water, Cyclopentasiloxane, Ethylhexyl Isononanoate, Butylene Glycol, Lauryl PEG-9 Polydimethylsiloxyethyl Dimethicone, Dimethicone, Phenoxyethanol, Sodium Chloride, Triethoxycaprylylsilane, Dimethicone/PEG-10/15 Crosspolymer, Dimethicone/Vinyl Dimethicone Crosspolymer, Iodopropynyl Butylcarbamate, Ascorbyl Palmitate, BHT, Retinyl Palmitate, Dipropylene Glycol, Zea Mays (Corn) Oil, Tocopherol

OTHER SAFETY INFORMATION

Protect the product in this container from excessive heat and direct sunlight